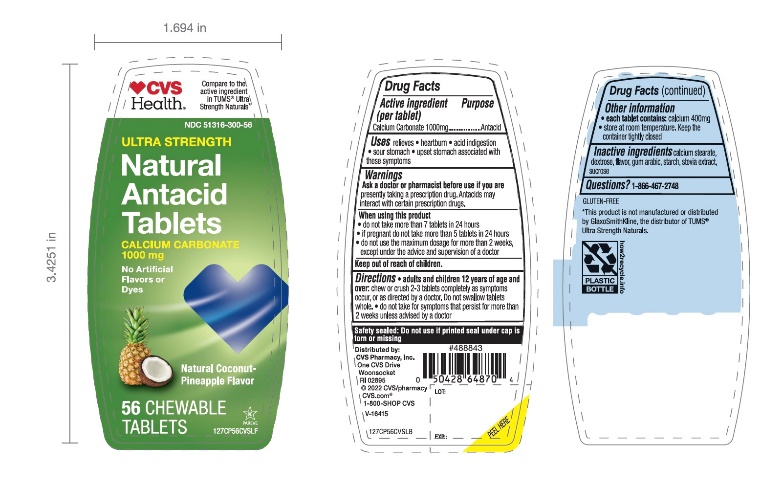 DRUG LABEL: CVS

NDC: 51316-300 | Form: TABLET, CHEWABLE
Manufacturer: CVS PHARMACY
Category: otc | Type: HUMAN OTC DRUG LABEL
Date: 20251208

ACTIVE INGREDIENTS: CALCIUM CARBONATE 1000 mg/1 1
INACTIVE INGREDIENTS: DEXTROSE, UNSPECIFIED FORM; ACACIA; STARCH, CORN; STEARIC ACID; STEVIA REBAUDIANA LEAF; SUCROSE

Drug Facts

Active ingredient (per tablet)

Calcium carbonate 1000 mg

Purpose

Antacid

Uses

relieves

- heartburn
- acid indigestion
- sour stomach
- upset stomach associated with these symptoms

Warnings

Ask a doctor or pharmacist before use if you are

presently taking a prescription drug. Antacids may interact with certain prescription drugs.

When using this product

- do not take more than 7 tablets in 24 hours
- If pregnant do not take more than 5 tablets in 24 hours
- do not use the maximum dosage for more than 2 weeks, except under the advice and supervision of a doctor

Directions

- adults and children 12 years of age and over:chew or crush 2-3 tablets completely as symptoms occur, or as directed by a doctor. Do not swallow tablets whole.
- do not take for symptoms that persist for more than 2 weeks unless advised by a doctor

Other information

- each tablet contains:calcium 400 mg
- Store at room temperature. Keep the container tightly closed

Inactive ingredients (Coconut Pineapple)

Dextrose, gum, Arabic, natural flavors, starch, stearic acid, stevia extract, sucrose,

Questions or comments?

1-866-467-2748

Principal Display Panel

*Compare to the active ingredient in Ultra Strength Tums Naturals

NDC 51316-300-56

ULTRA STRENGTH

Antacid Tablets

Calcium Carbonate 1000 mg

NO ARTIFICIAL FLAVORS OR DYES

Natural Coconut Pineapple Flavor

56CHEWABLE TABLETS

Do not use if printed inner safety seal under cap is broken or missing.

Distributed by:

*This product is not manufactured or distributed by GlaxoSmithKline, the distributer of Ultra Strength Tums Naturals.